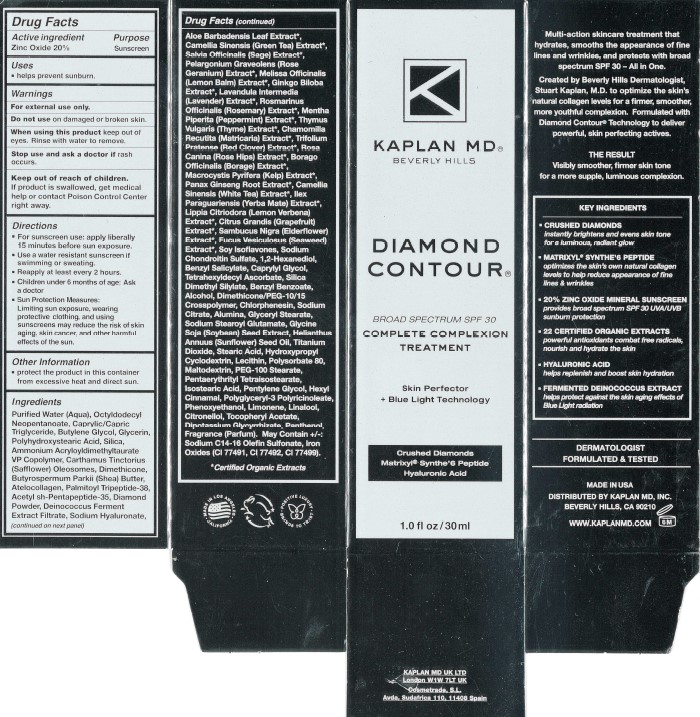 DRUG LABEL: Kaplan MD Diamond Contour Complete Complexion Treatment
NDC: 84300-003 | Form: CREAM
Manufacturer: Kaplan MD
Category: otc | Type: HUMAN OTC DRUG LABEL
Date: 20240514

ACTIVE INGREDIENTS: ZINC OXIDE 20 g/100 g
INACTIVE INGREDIENTS: SAGE; ROSA CANINA WHOLE; POLYHYDROXYSTEARIC ACID (2300 MW); ROSEMARY; MENTHA PIPERITA; THYME; PANAX GINSENG ROOT WATER; GRAPEFRUIT; TETRAHEXYLDECYL ASCORBATE; SODIUM C14-16 OLEFIN SULFONATE; CHLORPHENESIN; OCTYLDODECYL NEOPENTANOATE; PENTYLENE GLYCOL; PANTHENOL; LECITHIN, SOYBEAN; PENTAERYTHRITYL TETRAISOSTEARATE; ISOSTEARIC ACID; LINALOOL, (+/-)-; SOYBEAN; AMMONIUM ACRYLOYLDIMETHYLTAURATE/VP COPOLYMER; CARTHAMUS TINCTORIUS (SAFFLOWER) OLEOSOMES; SHEA BUTTER; ALOE VERA LEAF; CAPRYLYL GLYCOL; DIMETHICONE/PEG-10/15 CROSSPOLYMER; SODIUM CITRATE; TITANIUM DIOXIDE; STEARIC ACID; LIMONENE, (+/-)-; HYALURONATE SODIUM; BUTYLENE GLYCOL; FUCUS VESICULOSUS; BENZYL SALICYLATE; 1,2-HEXANEDIOL; BENZYL BENZOATE; ALCOHOL; PALMITOYL TRIPEPTIDE-38; SILICA DIMETHYL SILYLATE; SAMBUCUS NIGRA WHOLE; POLYSORBATE 80; GREEN TEA LEAF; BORAGE; SUNFLOWER OIL; PHENOXYETHANOL; GINKGO BILOBA WHOLE; ATELOCOLLAGEN; WATER; PELARGONIUM GRAVEOLENS WHOLE; SOY ISOFLAVONES; GLYCERIN; DIMETHICONE; MELISSA OFFICINALIS; RED CLOVER; MALTODEXTRIN; PEG-100 STEARATE; MACROCYSTIS PYRIFERA; SODIUM STEAROYL GLUTAMATE

Kaplan MD Diamond Contour Complete Complexion Treatment

Active Ingredient

Zinc Oxide 20%

Purpose

Sunscreen

Uses

Helps prevent sunburn.

Warnings

For external use only.

Do not use on damaged or broken skin.

When using this product keep out of eyes. Rinse with water to remove.

Stop use and ask a doctor if rash occurs.

Keep out of reach of children.

If product is swallowed, get medical help or contact Poison Control Center right away.

Directions

- For sunscreen use: apply liberally 15 minutes before sun exposure.
- Use a water resistant sunscreen if swimming or sweating.
- Reapply at least every 2 hours.
- Children under 6 months of age: Ask a doctor.
- Sun Protection Measures: Limiting sun exposure, wearing protective clothing, and using sunscreens may reduce the skin aging, skin cancer, and other harmful effects of the sun.

Other Information

Protect the product in this container from excessive heat and direct sun.

INACTIVE INGREDIENT

Purified Water (Aqua), Octyldodecyl Neopentanoate, Caprylic/Capric Triglyceride, Butylene Glycol, Glycerin, Polyhydroxystearic Acid, Silica, Ammonium Acryloyldimethyltaurate VP Copolymer, Carthamus Tinctorius (Safflower) Oleosomes, Dimethicone, Butyrospermum Parkii (Shea) Butter, Atelocollagen, Palmitoyl Tetrapeptide-38, Acetyl sh-Pentapeptide-35, Diamond Powder, Deinococcus Ferment Extract Filtrate, Sodium Hyaluronate, Aloe Barbadensis Leaf Extract*, Camellia Sinensis (Green Tea) Extract*, Salvia Officinalis (Sage) Extract*, Pelargonium Graveolens (Rose Geranium) Extract*, Melissa Officinalis (Lemon Balm) Extract*, Ginkgo Biloba Extract*, Lavandual Intermedia (Lavender) Extract*, Rosmarinus Officinalis (Rosemary) Extract*, Mentha Piperita (Peppermint) Extract*, Thymus Vulgaris (Thyme) Extract*, Chamomilla Recutita (Matricaria) Extract*, Trifolium Pratense (Red Clover) Extract*, Rosa Canina (Rose Hips) Extract*, Borago Officinalis (Borage) Extract*, Macrocystis Pyrifera (Kelp) Extract*, Panax Ginseng Root Extract*, Camellia Sinensis (White Tea) Extract*, Ilex Paraguariensis (Yerba Mate) Extract*, Lippia Citriodora (Lemon Verbena) Extract*, Citrus Grandis (Grapefruit) Extract*, Sambucus Nigra (Elderflower) Extract*, Fucus Vesiculosus (Seaweed) Extract*, Soy Isoflavones, Sodium Chondroitin Sulfate, 1,2-Hexanediol, Benzyl Salicylate, Caprylyl Glycol, Tetrahexyldecyl Ascorbate, Silica, Dimethyl Silylae, Benzyl Benzoate, Alcohol, Dimethicone/PEG-10/15 Crosspolymer, Chlorphenesin, Sodium Citrate, Alumina, Glyceryl Stearate, Sodium Stearoyl Glutamate, Glycine Soja (Soybean) Seed Extract, Helianthus Annuus (Sunflower) Seed Oil, Titanium Dioxide, Stearic Acid, Hydroxypropyl Cyclodextrin, Lecithin, Polysorbate 80, Maltodextrin, PEG-100 Stearate, Pentaerythrityl Tetraisostearate, Isostearic Acid, Pentylene Glycol, Hexyl Cinnamal, Polyglyceryl- Polyricinoleate, Phenoxyethanol, Limonene, Linalool, Citronellol, Tocopheryl Acetate, Dipotassium Glycyrrhizate, Panthenol, Fragrance (Parfum). May Contain +/-: Sodium C14-16 Olefin Sulfonate, Iron Oxides (CI 77491, CI 77492, CI 77499).

*Certified Organic Extracts